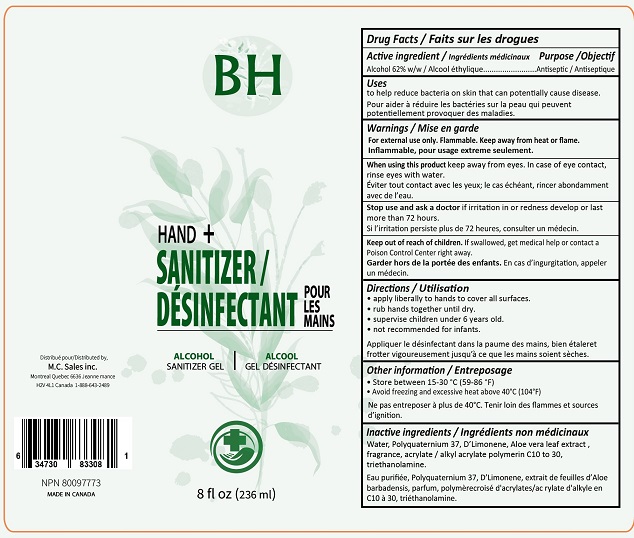 DRUG LABEL: BH Hand Sanitizer
NDC: 77454-116 | Form: GEL
Manufacturer: Location Et Ventes de t.v. Mid-Cite (2001) Inc.
Category: otc | Type: HUMAN OTC DRUG LABEL
Date: 20200508

ACTIVE INGREDIENTS: ALCOHOL 62 mL/100 mL
INACTIVE INGREDIENTS: CARBOMER INTERPOLYMER TYPE A (55000 CPS); POLYQUATERNIUM-37 (25000 MPA.S); ALOE VERA LEAF; TROLAMINE; LIMONENE, (+)-; WATER

BH Hand Sanitizer

Drug Facts

Active ingredient

Alcohol 62% w/w

Purpose

Antiseptic

Uses

to help reduce bacteria on skin that can potentially cause disease.

Warnings

For external use only. Flammable. Keep away from heat or flame.

When using this product keep away from eyes. In case of eye contact, rinse eyes with water.

Stop use and ask a doctor if irritation or redness develop or last more than 72 hours.

Keep out of reach of children. If swallowed, get medical help or contact a Poison Control Center right away.

Directions

- apply liberally to hands to cover all surfaces.
- rub hands together until dry.
- supervise children under 6 years old.
- not recommended for infants.

Other information

- Store between 15-30°C (59-86°F)
- Avoid freezing and excessive heat above 40°C (104°F)

Inactive ingredients

Water, Polyquaternium 37, D-Limonene, Aloe vera leaf extract, fragrance, acrylate / alkyl acrylate polymerin C10 to C30, triethanolamine.

Distributed by:

M.C. Sales inc.

Montreal Quebec 6636 Jeanne mance

H2V 4L1 Canada

1-888-643-2489

MADE IN CANADA

PACKAGE LABEL

BH
HAND + SANITIZER
ALCOHOL
SANITIZER GEL
8 fl oz (236 ml)